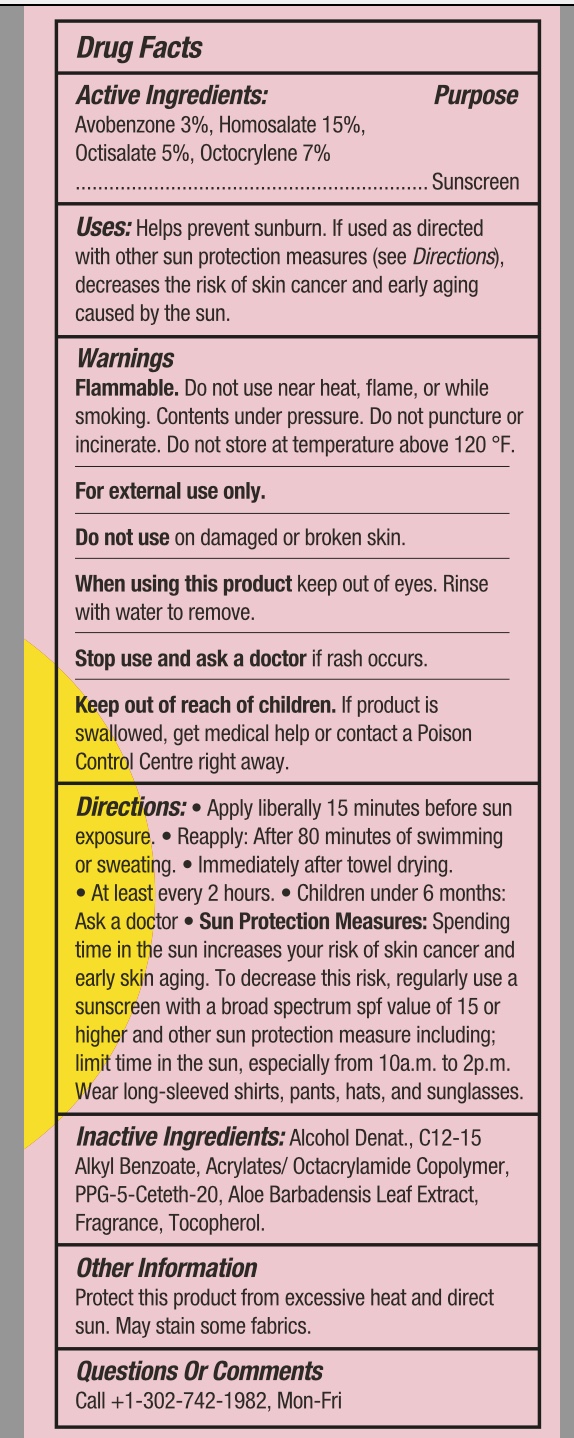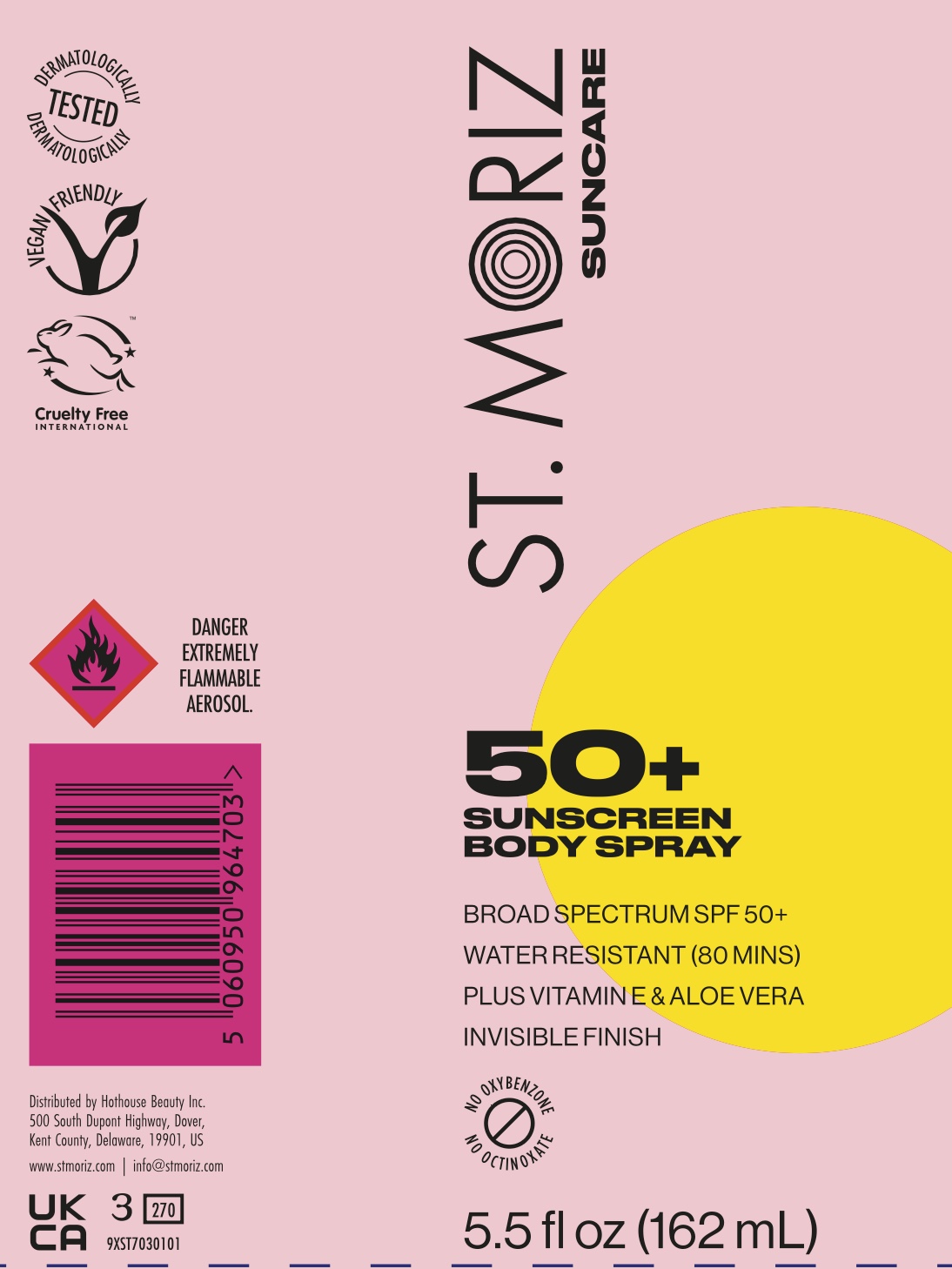 DRUG LABEL: St. Moriz Sunscreen Body
NDC: 85178-6095 | Form: SPRAY
Manufacturer: Hothouse Beauty Inc
Category: otc | Type: HUMAN OTC DRUG LABEL
Date: 20251126

ACTIVE INGREDIENTS: HOMOSALATE 150 mg/1 mL; OCTOCRYLENE 70 mg/1 mL; OCTISALATE 50 mg/1 mL; AVOBENZONE 30 mg/1 mL
INACTIVE INGREDIENTS: ALCOHOL; C12-15 ALKYL BENZOATE; PPG-5-CETETH-20; ALOE VERA LEAF; TOCOPHEROL; ACRYLATES/OCTYLACRYLAMIDE COPOLYMER (40000 MW)

St Moriz SPF 50 Sunscreen Body Spray

Drug Facts

85178-6095-0

Drug Facts

Active Ingredient

Homosalate 15%
Octocrylene 7.0%
Octisalate 5.0%
Avobenzone 3.0%

Purpose

Sunscreen

USES

- Helps Prevent Sunburn
- If Used As Directed With Other Sun Protection Measures (See Directions), Decreases The Risk Of Skin cancer And Early Skin Aging Caused By The Sun

Warnings

Flammable.Do not use near hear, flame, or while smoking. Contents under pressure. Do no puncture or incinerate. Do not store at temperature above 120oF

For external use only.

Do not use

on damaged or broken skin

When using this product

keep out of eyes. Rinse with water to remove

Stop use and ask a doctor

if rash occurs

K eep out of reach of children.

If product is swallowed, get medical help or contact a Poison Control Center right away

Directions

- apply liberally 15 minutes before sun exposure
- reapply after 80 minutes of swimming or sweating
- immediatelyafter towel drying
- at least every 2 hours
- children under month Ask a doctor
- Sun protectlon MeasuresSpending time In the sun increases your risk of skin cancer and early skin aging. To decrease this risk, regularly use a sunscreen with broad spectrum SPF of 15 or higher and other sun protection measures including: limit time in the sun, especially from 10 am-2pm. Wear Long-sleeve shirts, parts, hats, and sunglasses

Other Information

"Protect the product In this container from excessive heat or direct sun. May stain some fabrics.

Questions or Comments

Call +1-302-742-1982, Mon-Fri

Inactive Ingredients

Acrylates/Octacrylamide Copolymer, Alcohol Denat, Aloe Barbadensis Leaf Extract, C12-15 Alkyl Benzoate, Fragrance, PPG-5-Ceteth-20, Tocopherol

Package Principal Display Panel

85178-6095-0